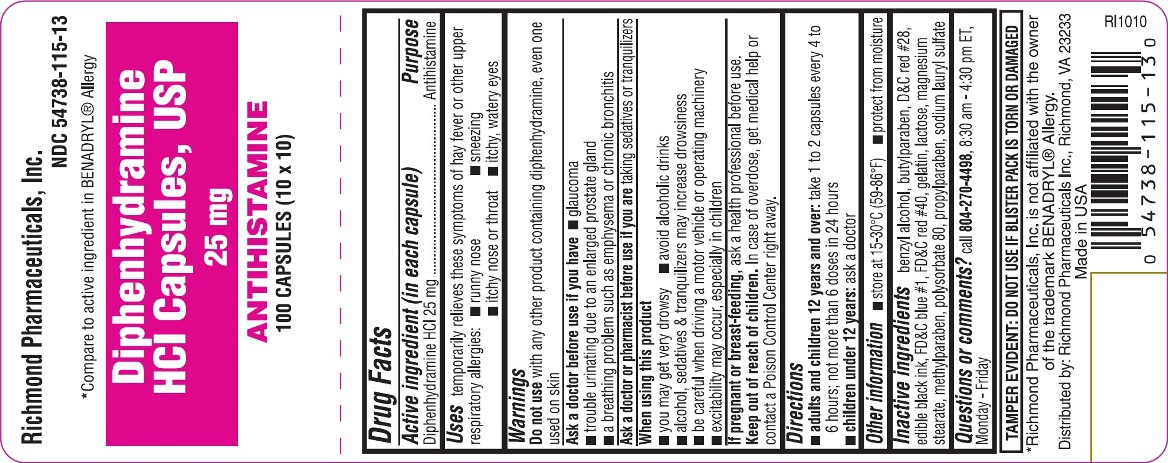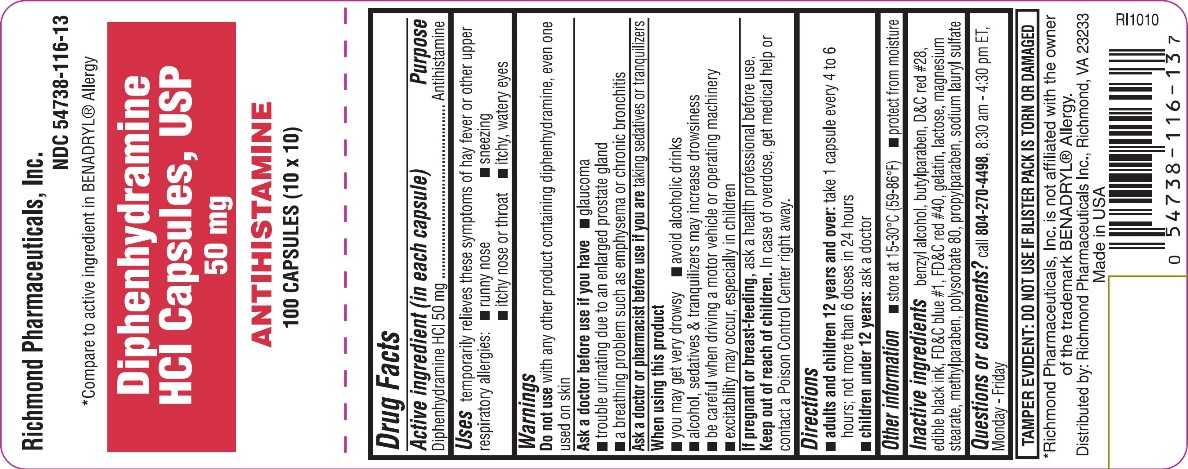 DRUG LABEL: Diphenhydramine Hydrochloride
NDC: 54738-115 | Form: CAPSULE
Manufacturer: Richmond Pharmaceuticals Inc.
Category: otc | Type: HUMAN OTC DRUG LABEL
Date: 20241226

ACTIVE INGREDIENTS: DIPHENHYDRAMINE HYDROCHLORIDE 25 mg/1 1
INACTIVE INGREDIENTS: BENZYL ALCOHOL; BUTYLPARABEN; D&C RED NO. 28; FD&C BLUE NO. 1; FD&C RED NO. 40; GELATIN; LACTOSE; MAGNESIUM STEARATE; METHYLPARABEN; POLYSORBATE 80; PROPYLPARABEN; SODIUM LAURYL SULFATE

Diphenhydramine HCl Capsules, USP

Drug Facts

Active ingredient

(in each capsule)

Diphenhydramine HCl 25 mg

Purpose

Antihistamine

Uses

temporarily relieves these symptoms of hay fever or other upper respiratory allergies:

- runny nose
- sneezing
- itchy nose or throat
- itchy, watery eyes

Warnings

Do not use with any other product containing diphenhydramine, even one used on skin

Ask a doctor before use if you have

- glaucoma
- trouble urinating due to an enlarged prostate gland
- a breathing problem such as emphysema or chronic bronchitis

Ask a doctor or pharmacist before use if you are

taking sedatives or tranquilizers

When using this product

- you may get very drowsy
- avoid alcoholic drinks
- alcohol, sedatives & tranquilizers may increase drowsiness
- be careful when driving a motor vehicle or operating machinery
- excitability may occur, especially in children

If pregnant or breast-feeding,

ask a health professional before use.

Keep out of reach of children.

In case of overdose, get medical help or contact a Poison Control Center right away.

Directions

- adults and children 12 years and over:take 1 to 2 capsules every 4 to 6 hours; not more than 6 doses in 24 hours
- children under 12 years:ask a doctor

Other information

- store at 15-30°C(59-86°F)
- protect from moisture

Inactive ingredients

benzyl alcohol, butylparaben, D&C red #28, edible black ink, FD&C blue #1, FD&C red #40, gelatin, lactose, magnesium stearate, methylparaben, polysorbate 80, propylparaben, sodium lauryl sulfate

Questions or comments?

call 804-270-4498, 8:30 am - 4:30 pm ET, Monday – Friday

TAMPER EVIDENT: DO NOT USE IF BLISTER PACK IS TORN OR DAMAGED

*Richmond Pharmaceuticals, Inc. is not affiliated with the owner of the trademark BENADRYL® Allergy.

Distributed by: Richmond Pharmaceuticals Inc., Richmond, VA 23233 Made in USA

RI1010

Principle Display Panel

Richmond Pharmaceuticals, Inc.

*Compare to active ingredient in BENADRYL® Allergy

Diphenhydramine HCI Capsules, USP

25 mg
50 mg

ANTIHISTAMINE

100 CAPSULES (10 x 10)